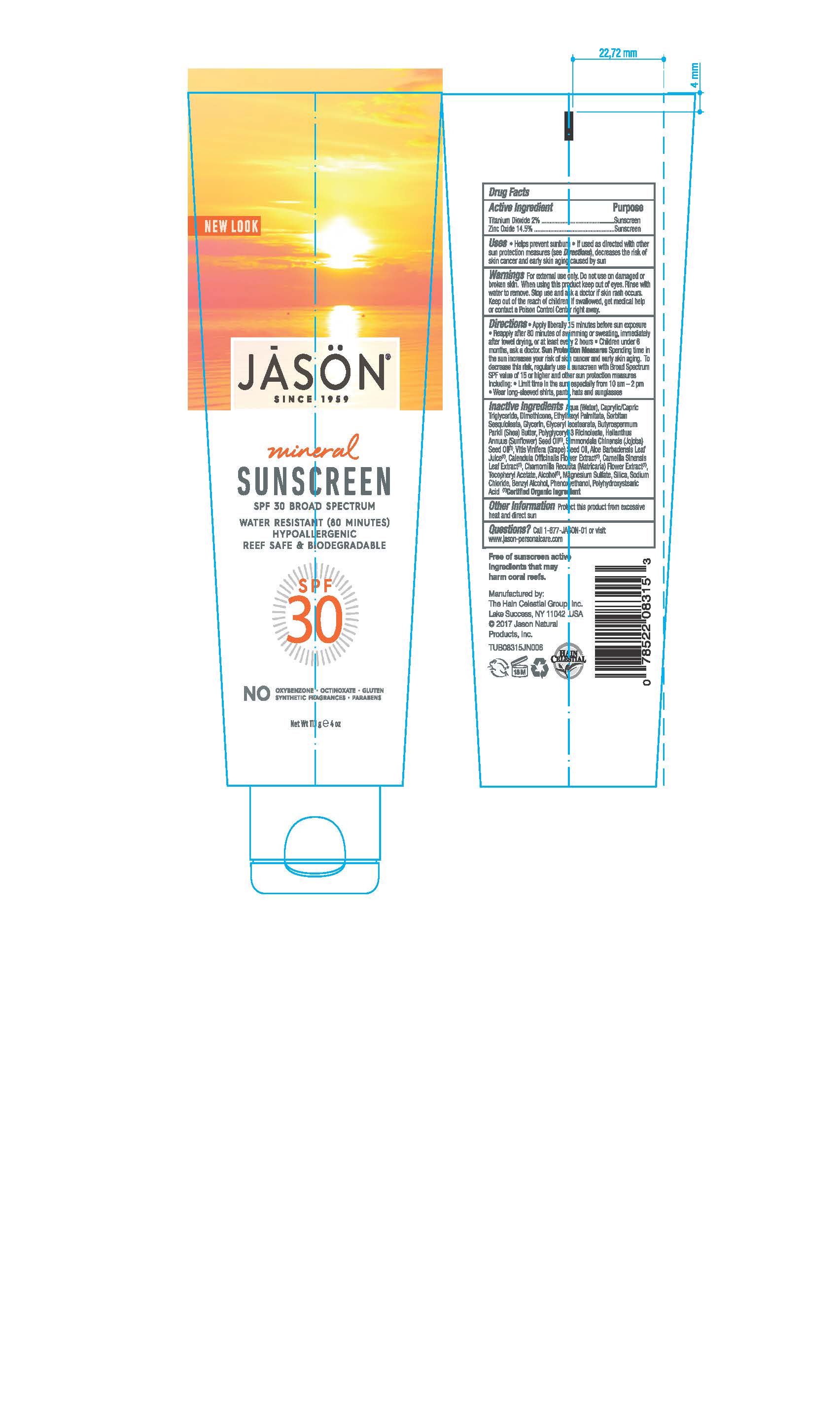 DRUG LABEL: Jason Mineral Sunscreen SPF30 Broad Spectrum
NDC: 61995-0015 | Form: CREAM
Manufacturer: The Hain Celestial Group, Inc.
Category: otc | Type: HUMAN OTC DRUG LABEL
Date: 20210412

ACTIVE INGREDIENTS: ZINC OXIDE 14.5 g/100 g; TITANIUM DIOXIDE 2 g/100 g
INACTIVE INGREDIENTS: GREEN TEA LEAF; JOJOBA OIL; SORBITAN SESQUIOLEATE; GLYCERIN; DIMETHICONE; PHENOXYETHANOL; SHEA BUTTER; POLYGLYCERYL-3 RICINOLEATE; .ALPHA.-TOCOPHEROL ACETATE; ALCOHOL; SILICON DIOXIDE; WATER; MEDIUM-CHAIN TRIGLYCERIDES; ETHYLHEXYL PALMITATE; GLYCERYL ISOSTEARATE; ALOE; CALENDULA OFFICINALIS FLOWER; MAGNESIUM SULFATE, UNSPECIFIED FORM; POLYHYDROXYSTEARIC ACID (2300 MW); SODIUM CHLORIDE; CHAMOMILE; SUNFLOWER OIL; GRAPE SEED OIL; BENZYL ALCOHOL

Jason Mineral Sunscreen SPF30 Broad Spectrum

ACTIVE INGREDIENT

Titanium Dioxide 2.0%

Zinc Oxide 14.5%

INDICATIONS AND USAGE

Helps prevent sunburns. If used as directed with other sun protection measures decreases the risk of skin cancer and skin aging caused by the sun. Sun Protection Measures: Spending time on the sun increases your risk of skin cancer and skin aging. To decrease the risk regulary use Broad Spectrum Sunscreen with SPF 15 or higher and other protective measures including: limit time in sun, especially from 10am to 2 pm, and wear long-sleeved shirts, pants, hats ans sunglasses.

WARNINGS

For external use only. Do not use on damaged or broken skin. When using this product keep out of eyes. Rinse with water to remove. Stop use and ask a doctor if skin rash occurs.

PURPOSE

Sunscreen

Keep out of reach of children. If swallowed, get medical help or contact Poison Control Center right away.

INACTIVE INGREDIENT

Water, Caprylic/Capric Triglyceride, Dimethicone, Ethyhexyl Palmitate, Sorbitan Sesquioleate, Glycerin, Glyceryl Isostearate, Butyrospermum PARKII (Shea Butter), Polyglyceryl-3 Ricinoleate, Helianthus Annuus (Sunflower) Seed Oil (1), Simmondsia Chinensis (Jojoba) Seed Oil (1), Vitis Vinifera(Grape) Seed Oil, Aloe Barbadensis Leaf Juice (1), Calendula Officinalis Flower Extract (1), Chamomilla Recutita (Matricaria) Flower Extract (1), Tocopheryl Acetate, Alcohol, Magnesium Sulfate, Silica, Sodium Chloride, Benzyl Alcohol, Phenoxyethanol, Polyxydroxystearic Acid.